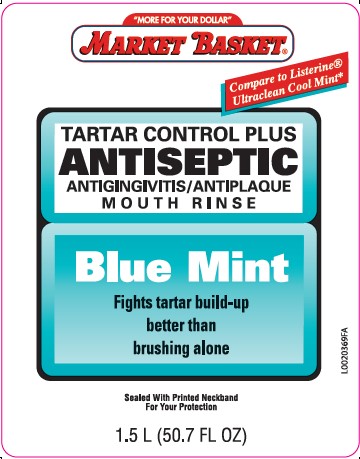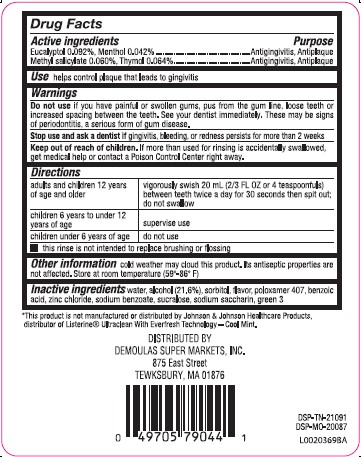 DRUG LABEL: Eucalyptol, menthol, methyl salicylate, thymol
NDC: 53942-855 | Form: MOUTHWASH
Manufacturer: Demoulas Super Markets, Inc
Category: otc | Type: HUMAN OTC DRUG LABEL
Date: 20260203

ACTIVE INGREDIENTS: EUCALYPTOL 0.92 mg/1 mL; MENTHOL 0.42 mg/1 mL; METHYL SALICYLATE 0.6 mg/1 mL; THYMOL 0.64 mg/1 mL
INACTIVE INGREDIENTS: WATER; ALCOHOL; SORBITOL; POLOXAMER 407; BENZOIC ACID; ZINC CHLORIDE; SODIUM BENZOATE; SUCRALOSE; SACCHARIN SODIUM; FD&C GREEN NO. 3

Market Basket 855.000/855AA-AC
Tartar Control Plus Antiseptic Mouth Rinse, Blue Mint

Active ingredient

Eucalyptol 0.092%

Menthol 0.042%

Methyl salicylate 0.060%

Thymol 0.064%

Purpose

Antigingivitis, antiplaque

Use

helps control plaque that leads to gingivitis

Warnings

for this product

Do not use

if you have painful or swollen gums, pus from the gum line, loose teeth or increased spacing between the teeth. See your dentist immediately. These may be signs of periodontitis, a serious form of gum disease.

Stop use and ask a dentist if

gingivitis, bleeding, or redness persists for more than 2 weeks

Keep out of reach of children.

If more than used for rinsing is accidentally swallowed, get medical help or contact a Poison Control Center right away.

Directions

adults and children 12 years of age and older - vigorously swish 20 mL (2/3 FL OZ or 4 teaspoonfuls) between teeth twice a day for 30 seconds then spit out; do not swallow

children 6 years to under 12 years of age - supervise use

children under 6 years of age - do not use

- this rinse is not intended to replace brushing or flossing

Other information

cold weather may cloud this product. Its antiseptic properties are not affected. Store at room temperature (59°-86°F)

Inactive ingredients

water, alcohol 21.6%, sorbitol, flavor, poloxamer 407, benzoic acid, zinc chloride, sodium benzoate, sucralose, sodium saccharin, green 3

ADVERSE REACTION

*This product is not manufactured or distributed by Johnson & Johnson Healthcare products, distributor of Listerine®Ultraclean With Everfresh Technology - Cool Mint.

DISTRIBUTED BY

DEMOULAS SUPER MARKETS, INC.

875 East Street

TEWKSBURY, MA 01876

DSP-TN-21091

DSP-MO-20087

Principal display panel

"MORE FOR YOUR DOLLAR"

MARKET BASKET®

Compare to Listerine®Ultraclean Cool Mint*

TARTAR CONTROL PLUS

ANTISEPTIC

ANTIGINGIVITIS/ANTIPLAQUE

MOUTH RINSE

Blue Mint

Fights tartar build-up

better than

brushing alone

Sealed With Printed Neckband For Your Protection

1.5 L (50.7 FL OZ)